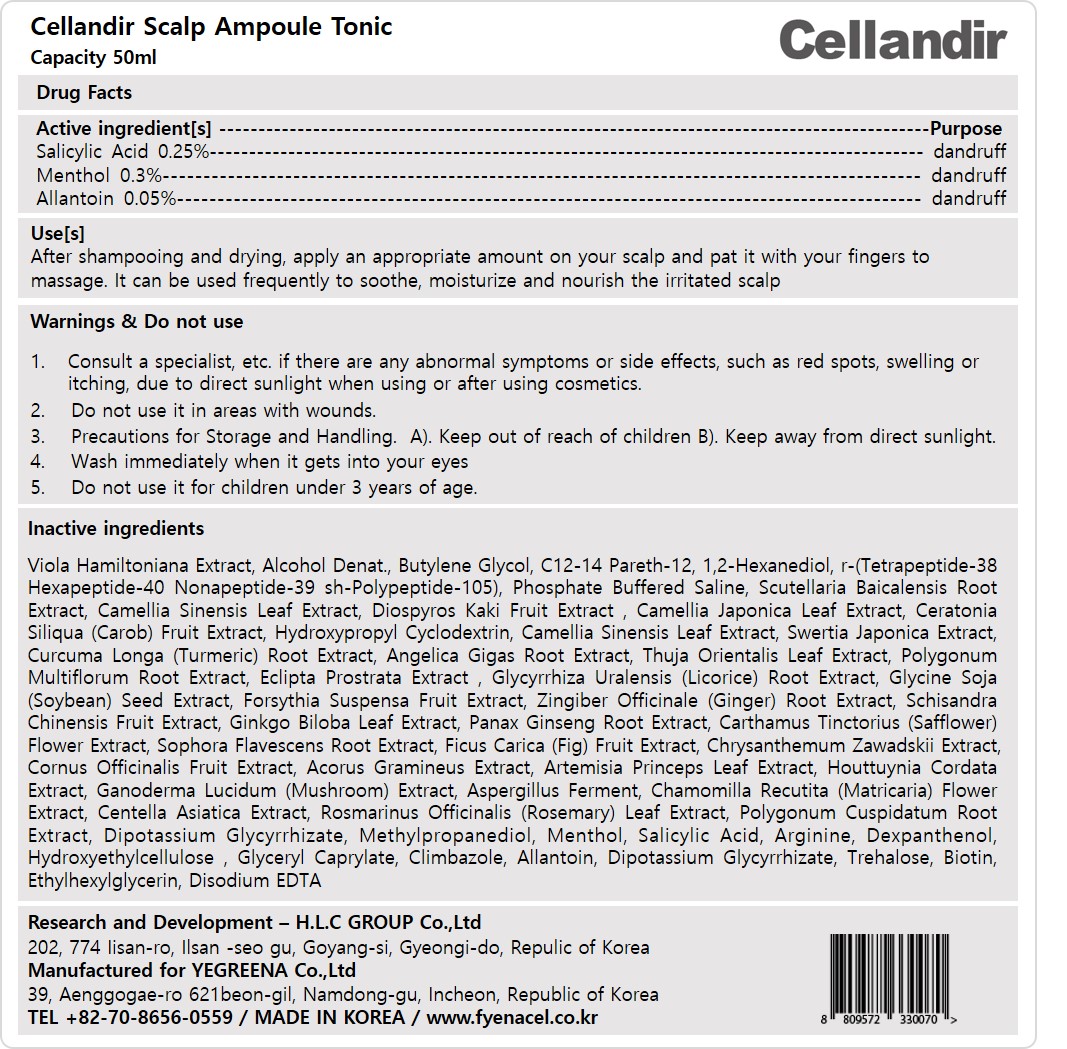 DRUG LABEL: CELLANDIR SCALP AMPOULE
NDC: 81555-202 | Form: LIQUID
Manufacturer: H.L.C GROUP Co., ltd
Category: otc | Type: HUMAN OTC DRUG LABEL
Date: 20231124

ACTIVE INGREDIENTS: MENTHOL, UNSPECIFIED FORM 0.3 mg/100 mL; SALICYLIC ACID 0.25 mg/100 mL; ALLANTOIN 0.05 mg/100 mL
INACTIVE INGREDIENTS: CAMELLIA JAPONICA LEAF; TURMERIC; PLATYCLADUS ORIENTALIS LEAF; ECLIPTA PROSTRATA LEAF; GLYCYRRHIZA URALENSIS ROOT; GINGER; SAFFLOWER; ACORUS GRAMINEUS ROOT; ARTEMISIA PRINCEPS LEAF; CENTELLA ASIATICA WHOLE; REYNOUTRIA JAPONICA ROOT; GLYCYRRHIZINATE DIPOTASSIUM; METHYLPROPANEDIOL; HYDROXYETHYL CELLULOSE, UNSPECIFIED; GLYCERYL MONOCAPRYLATE; ETHYLHEXYLGLYCERIN; ALCOHOL; BUTYLENE GLYCOL; 1,2-HEXANEDIOL; SCUTELLARIA BAICALENSIS ROOT; SOYBEAN; ROSEMARY; BIOTIN; TREHALOSE; C12-14 PARETH-12; SOPHORA FLAVESCENS ROOT; REISHI; HOUTTUYNIA CORDATA FLOWERING TOP; SWERTIA JAPONICA WHOLE FLOWERING; ANGELICA GIGAS ROOT; GINKGO; ARGININE; PANTHENOL; EDETATE DISODIUM ANHYDROUS; REYNOUTRIA MULTIFLORA ROOT; PERSIMMON; CAROB; HYDROXYPROPYL BETADEX; FORSYTHIA SUSPENSA FRUIT; CORNUS OFFICINALIS FRUIT; CHRYSANTHEMUM ZAWADSKII WHOLE; CHAMOMILE; SCHISANDRA CHINENSIS FRUIT; ASIAN GINSENG; FIG; CLIMBAZOLE; GREEN TEA LEAF

81555-202 CELLANDIR SCALP AMPOULE

Active ingredient[s]

Salicylic Acid 0.25%

Menthol 0.3%

Allantoin 0.05%

Purpose

dandruff

Use[s]

Cellandir scalp ampoule tonic is a functional product for relieving hair loss symptoms and improving the scalp environment, which efficiently delivers effective ingredients to the scalp.

Warnings

Precautions for Storage and Handling.

Keep away from direct sunlight.

Wash immediately when it gets into your eyes

Do not use it in areas with wounds.

Do not use it for children under 3 years of age.

Stop use and ask a doctor

Consult a specialist, etc. if there are any abnormal symptoms or side effects, such as red spots, swelling or itching, due to direct sunlight when using or after using cosmetics.

Keep out of reach of children

Directions

After shampooing and drying, apply an appropriate amount on your scalp and pat it with your fingers to massage. It can be used frequently to soothe, moisturize and nourish the irritated scalp.

Inactive ingredients

Viola Hamiltoniana Extract, Alcohol Denat., Butylene Glycol, C12-14 Pareth-12, 1,2-Hexanediol, r-(Tetrapeptide-38 Hexapeptide-40 Nonapeptide-39 sh-Polypeptide-105), Phosphate Buffered Saline, Scutellaria Baicalensis Root Extract, Camellia Sinensis Leaf Extract, Diospyros Kaki Fruit Extract , Camellia Japonica Leaf Extract, Ceratonia Siliqua (Carob) Fruit Extract, Hydroxypropyl Cyclodextrin, Camellia Sinensis Leaf Extract, Swertia Japonica Extract, Curcuma Longa (Turmeric) Root Extract, Angelica Gigas Root Extract, Thuja Orientalis Leaf Extract, Polygonum Multiflorum Root Extract, Eclipta Prostrata Extract , Glycyrrhiza Uralensis (Licorice) Root Extract, Glycine Soja (Soybean) Seed Extract, Forsythia Suspensa Fruit Extract, Zingiber Officinale (Ginger) Root Extract, Schisandra Chinensis Fruit Extract, Ginkgo Biloba Leaf Extract, Panax Ginseng Root Extract, Carthamus Tinctorius (Safflower) Flower Extract, Sophora Flavescens Root Extract, Ficus Carica (Fig) Fruit Extract, Chrysanthemum Zawadskii Extract, Cornus Officinalis Fruit Extract, Acorus Gramineus Extract, Artemisia Princeps Leaf Extract, Houttuynia Cordata Extract, Ganoderma Lucidum (Mushroom) Extract, Aspergillus Ferment, Chamomilla Recutita (Matricaria) Flower Extract, Centella Asiatica Extract, Rosmarinus Officinalis (Rosemary) Leaf Extract, Polygonum Cuspidatum Root Extract, Dipotassium Glycyrrhizate, Methylpropanediol, Menthol, Salicylic Acid, Arginine, Dexpanthenol, Hydroxyethylcellulose , Glyceryl Caprylate, Climbazole, Allantoin, Dipotassium Glycyrrhizate, Trehalose, Biotin, Ethylhexylglycerin, Disodium EDTA